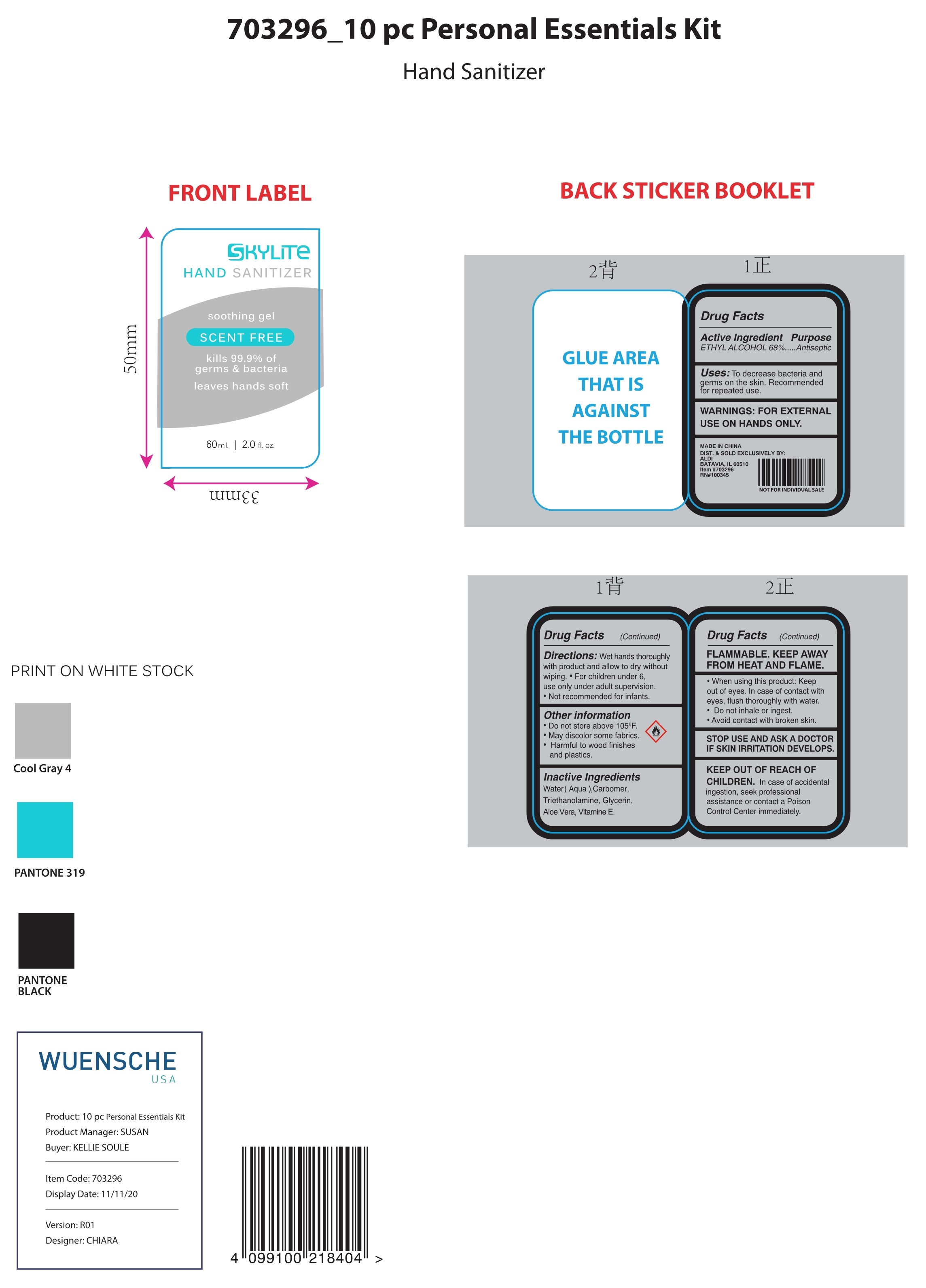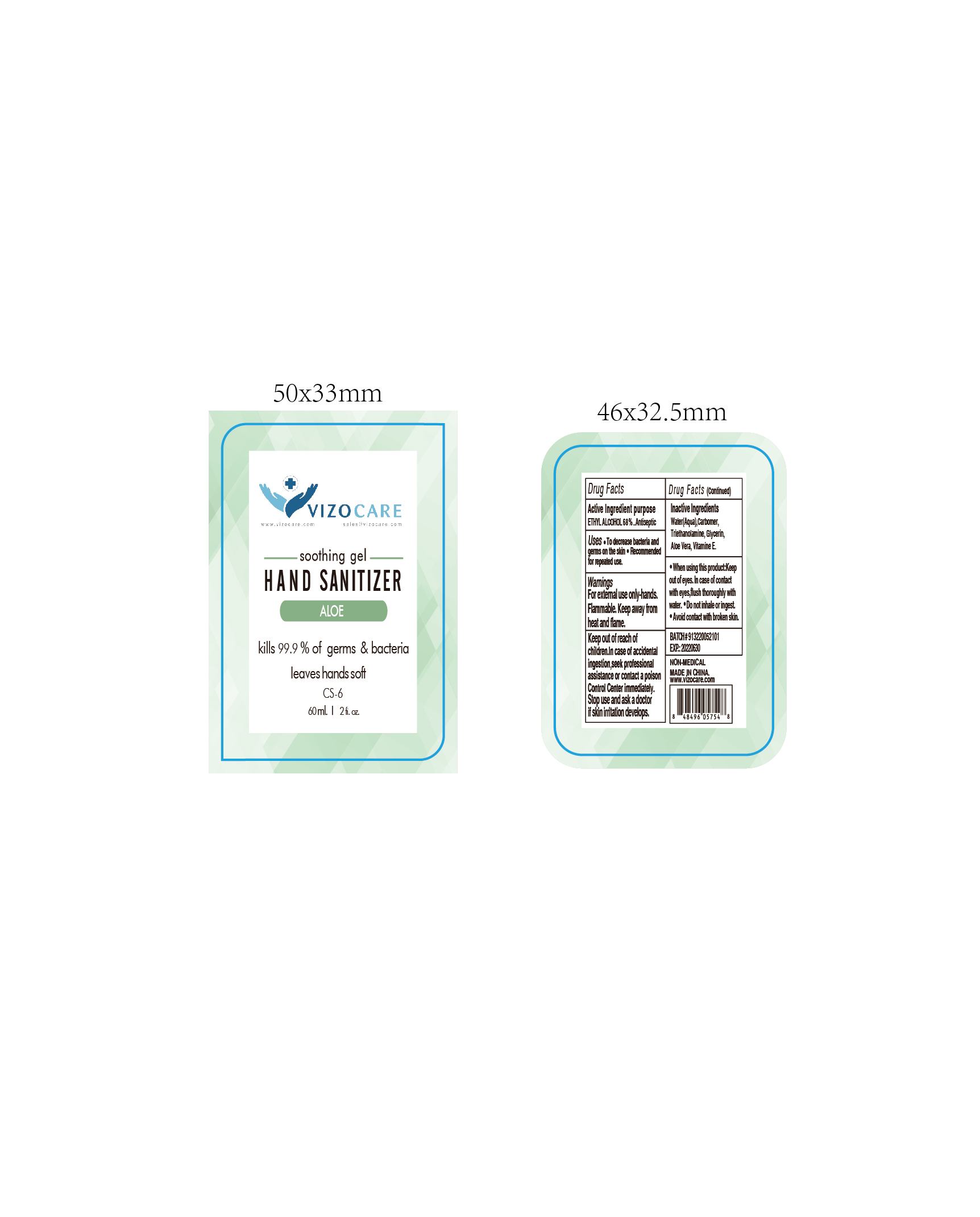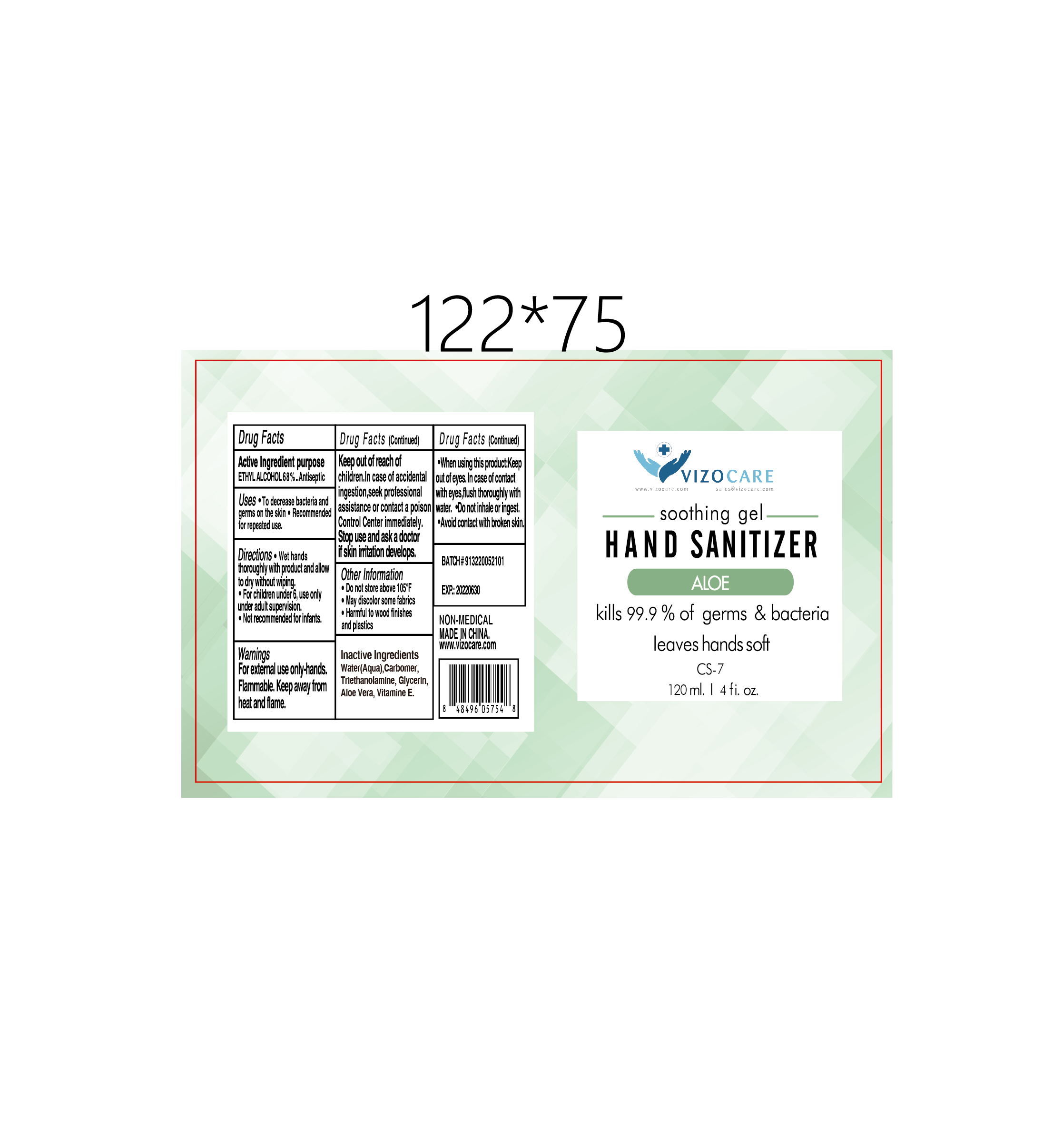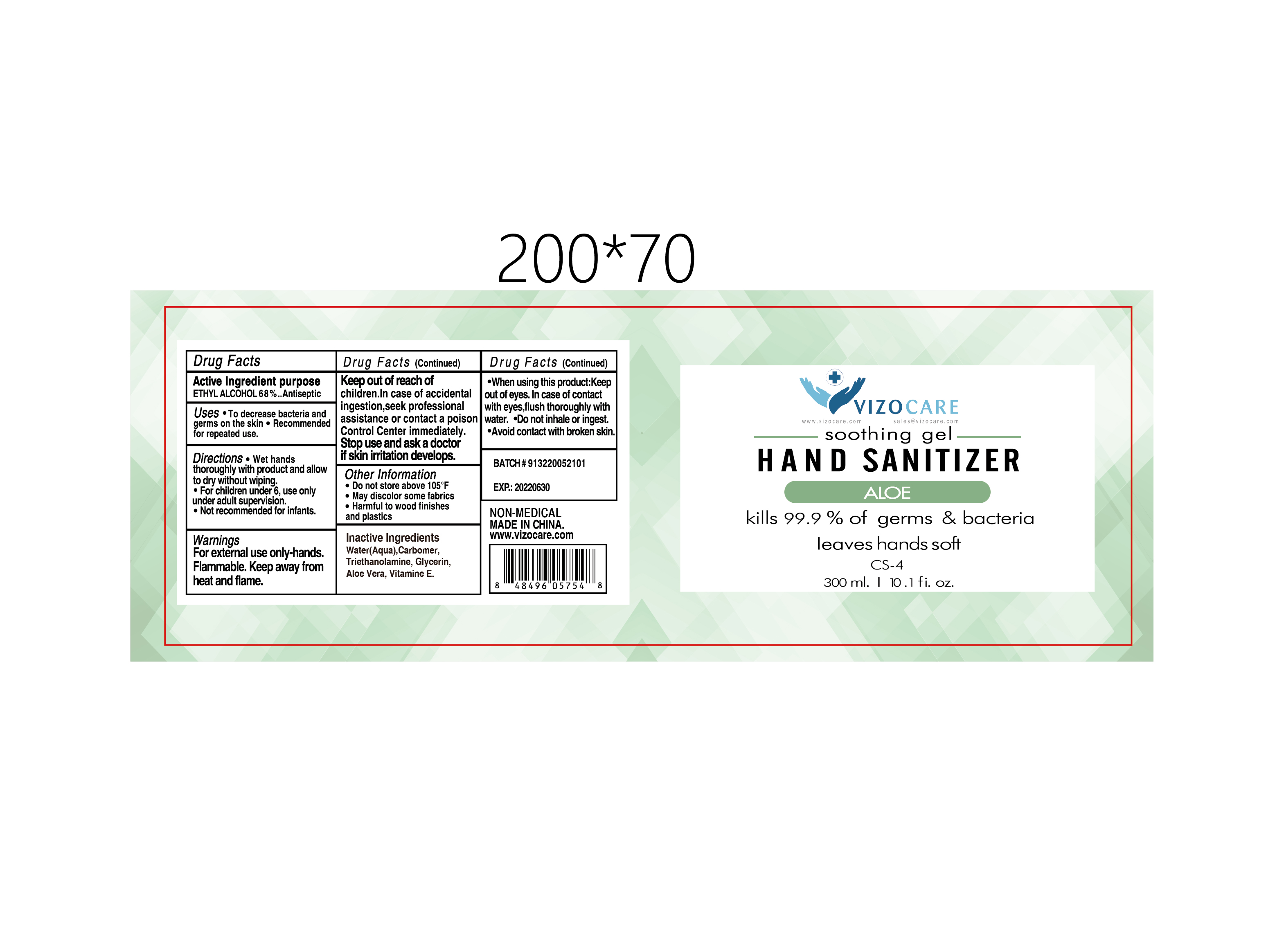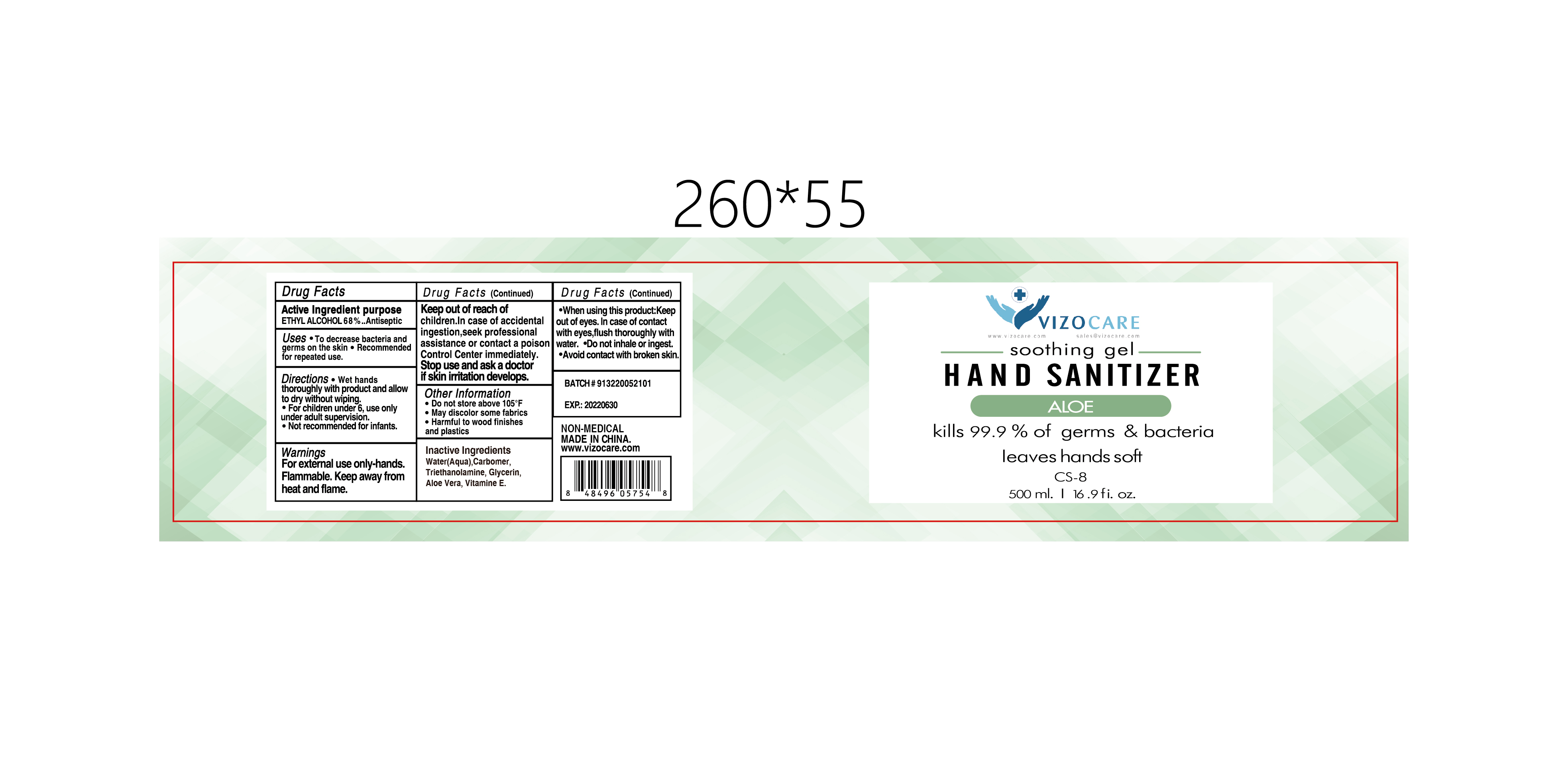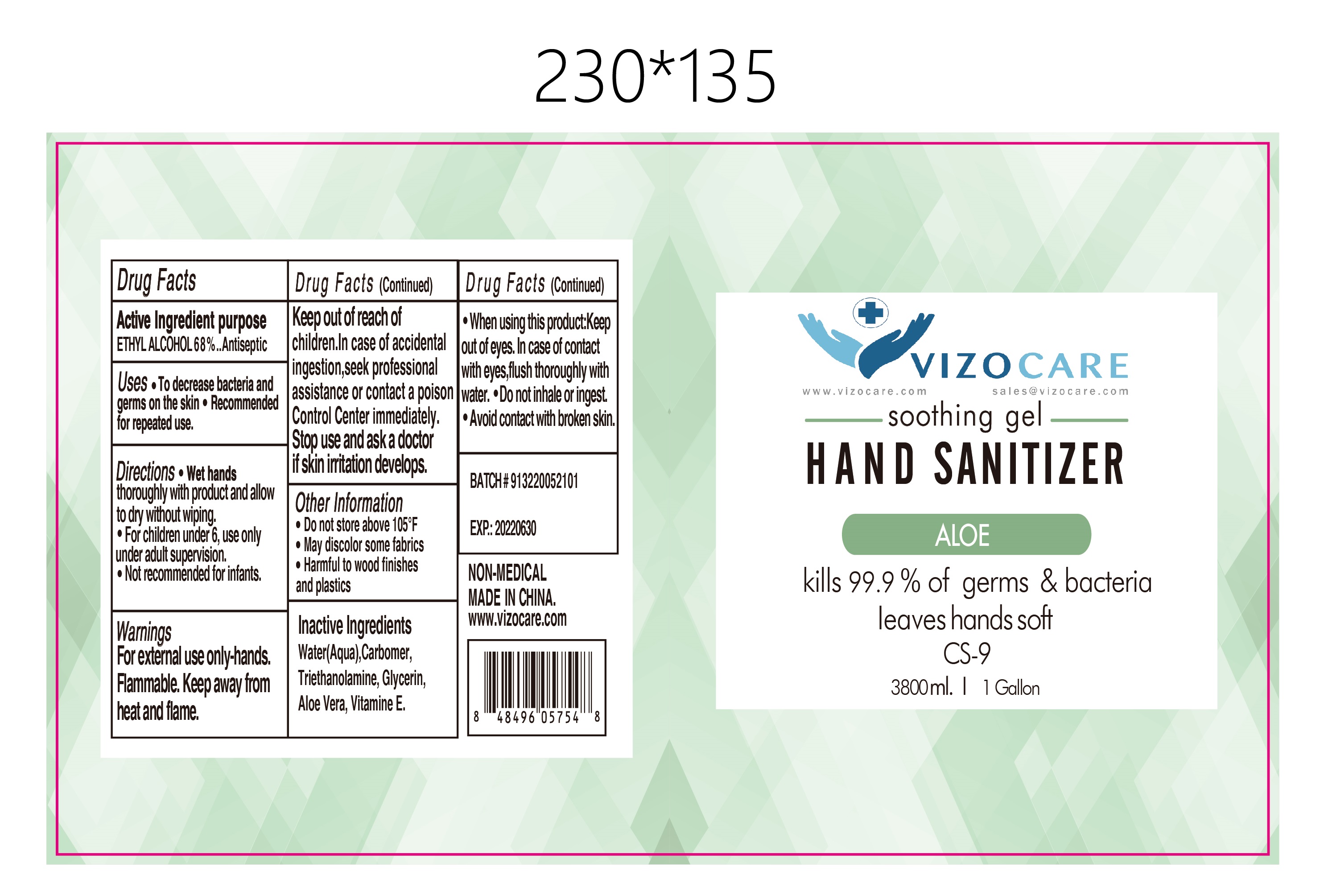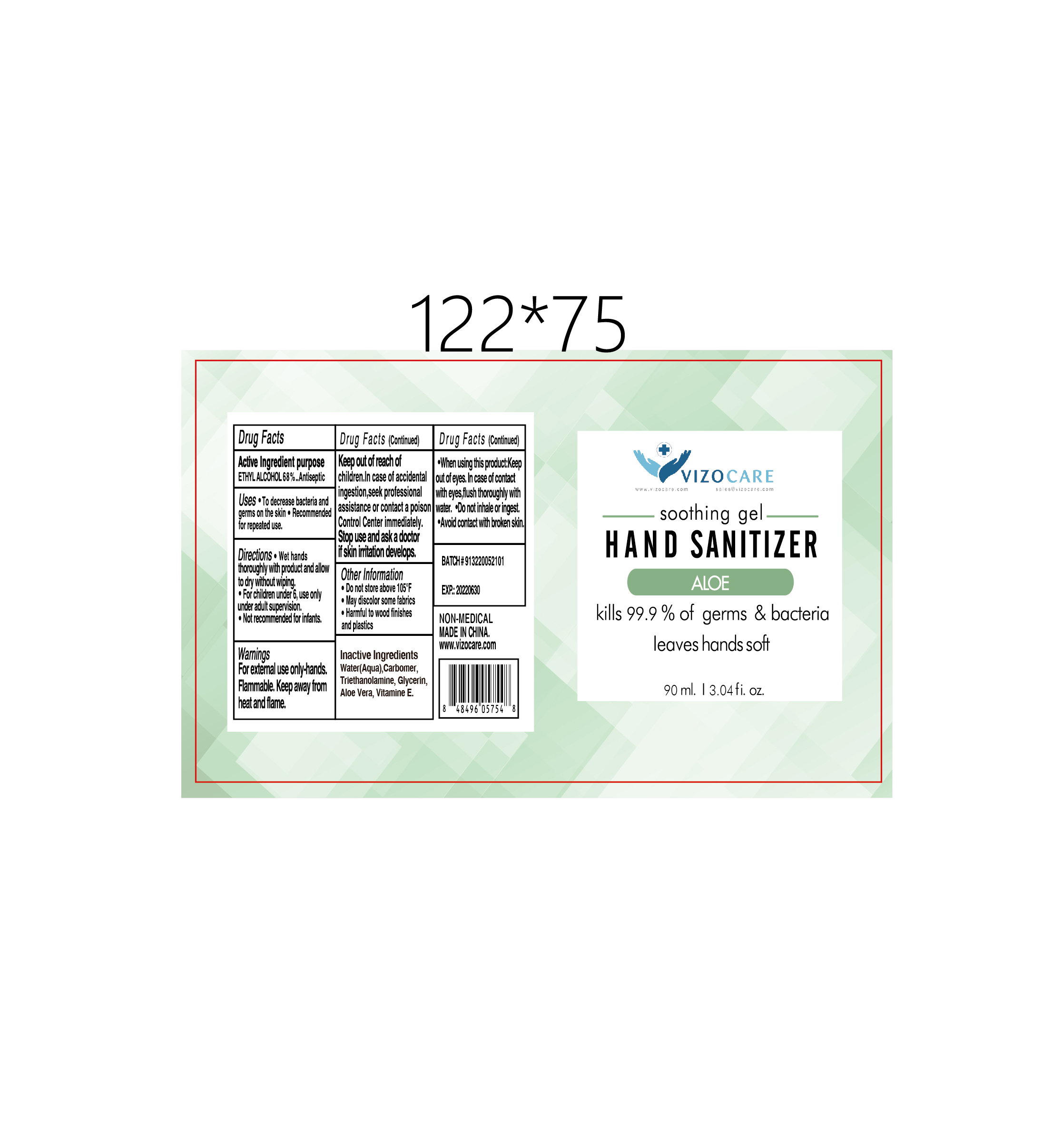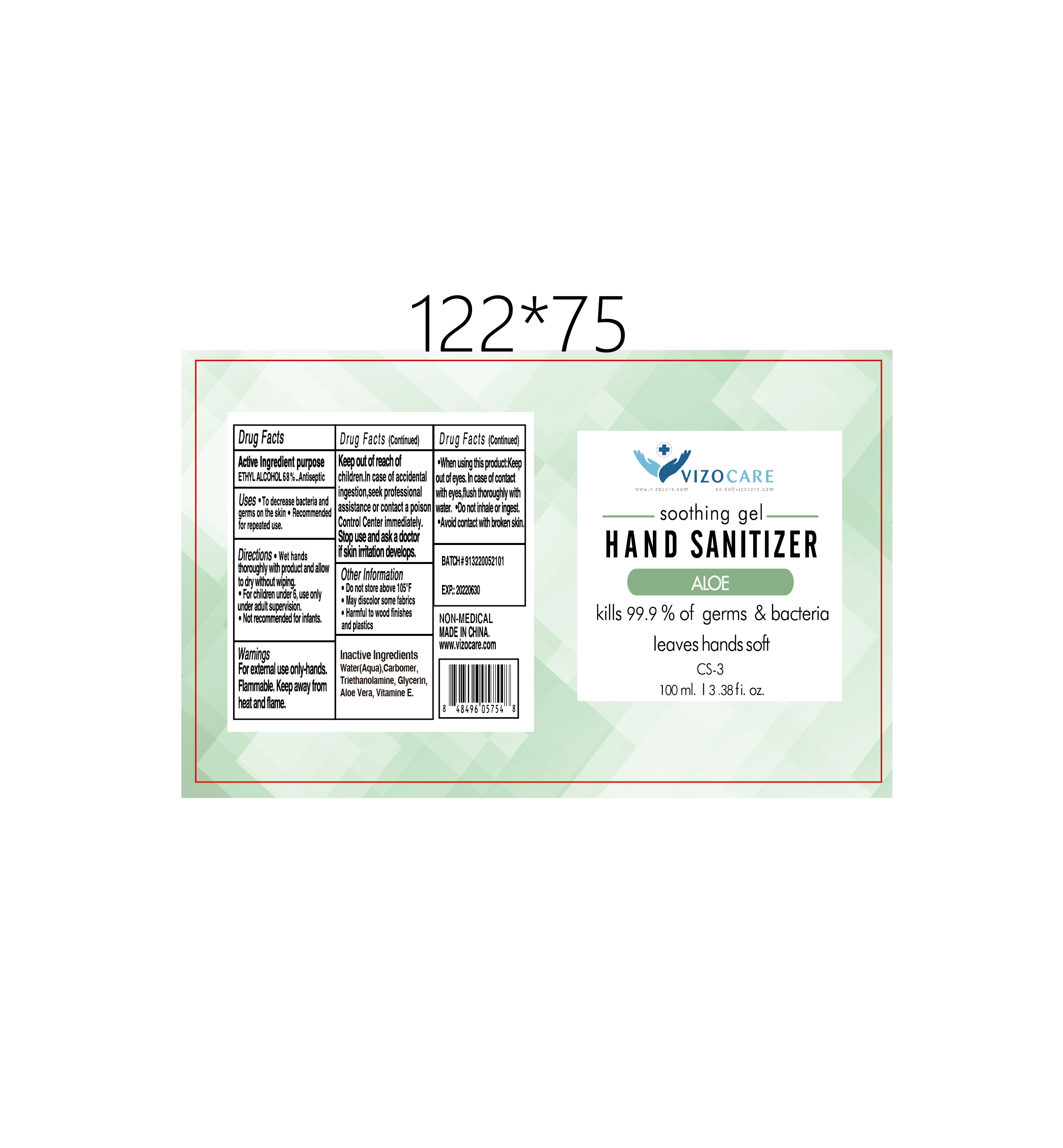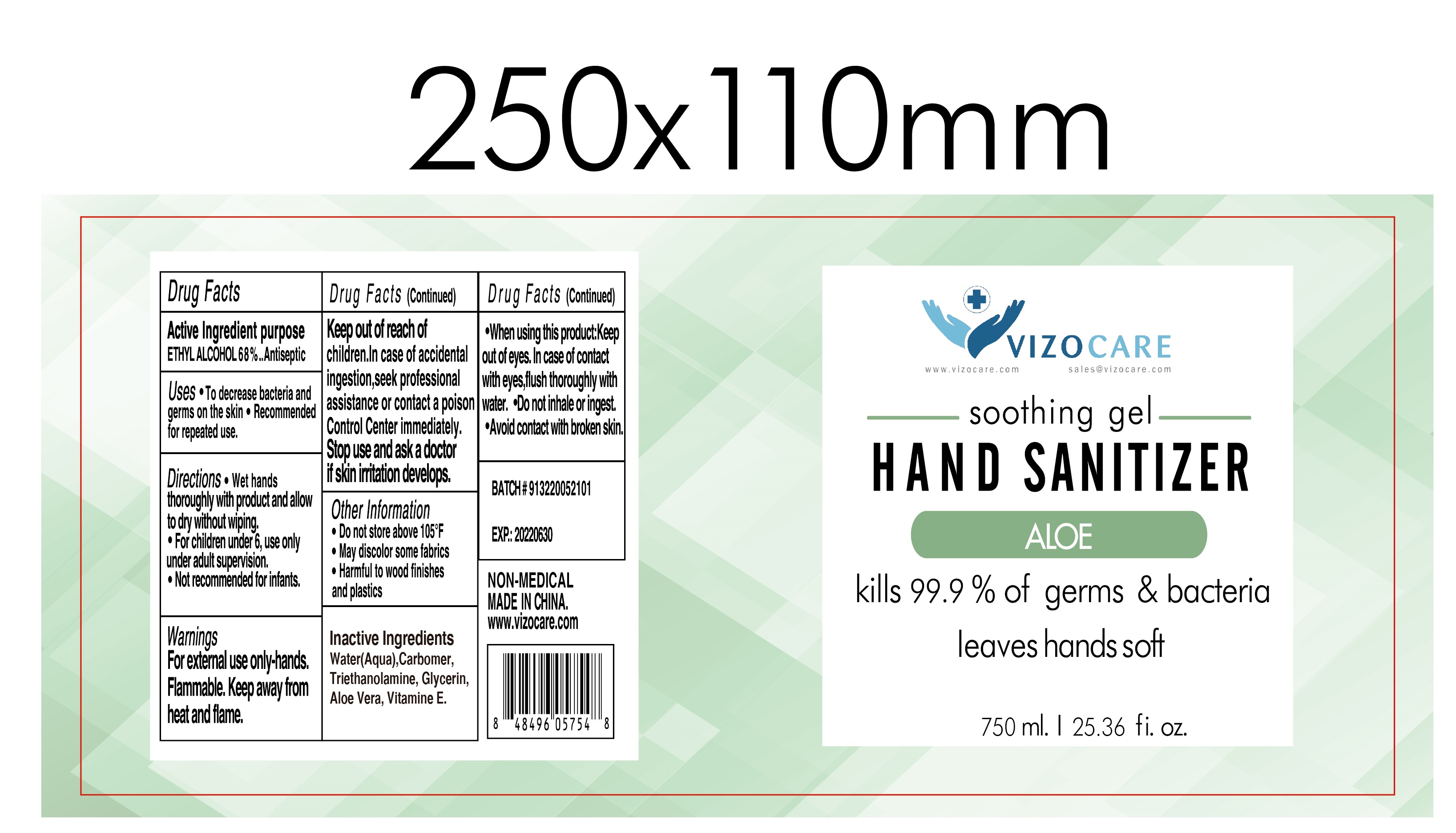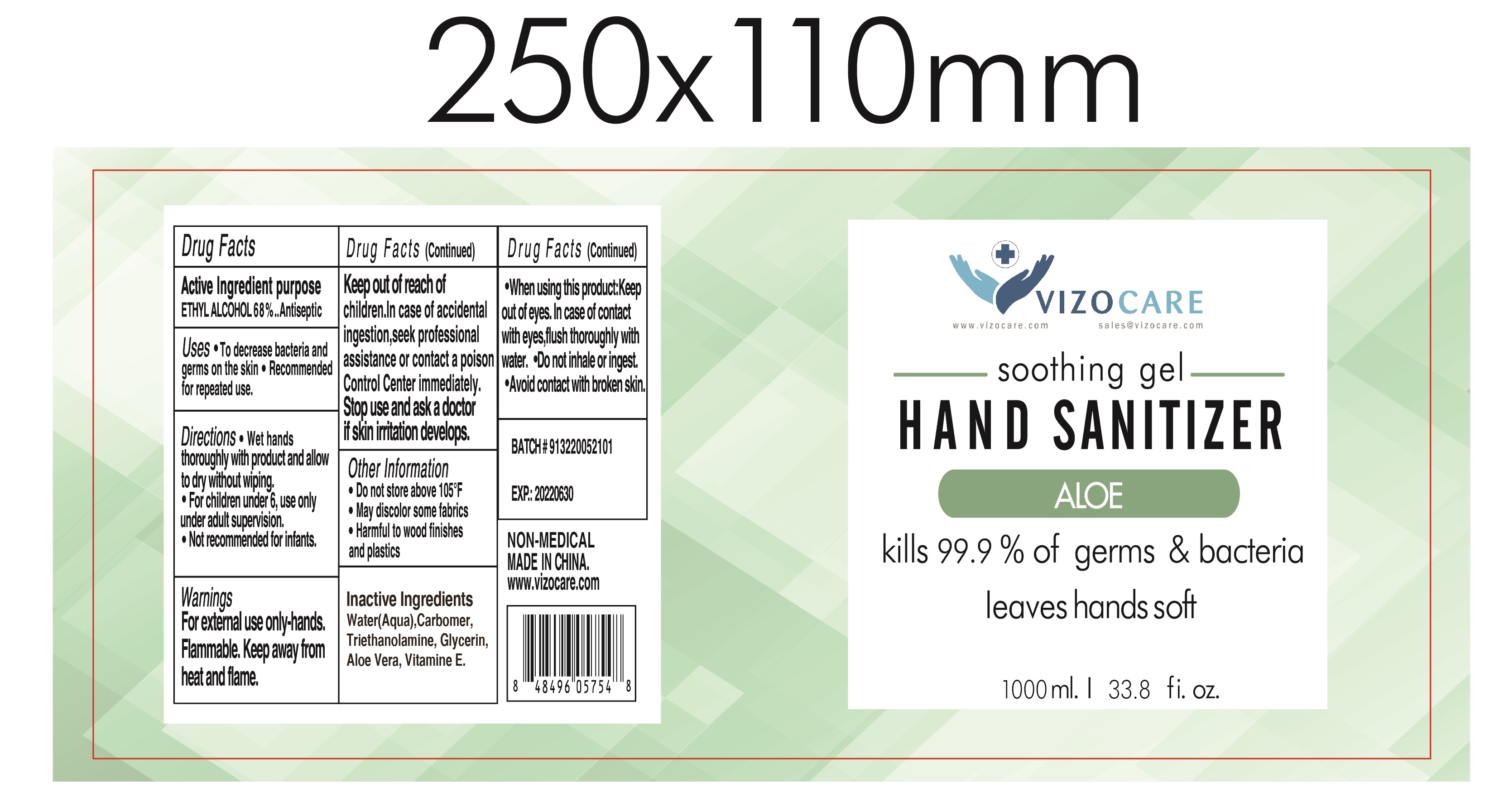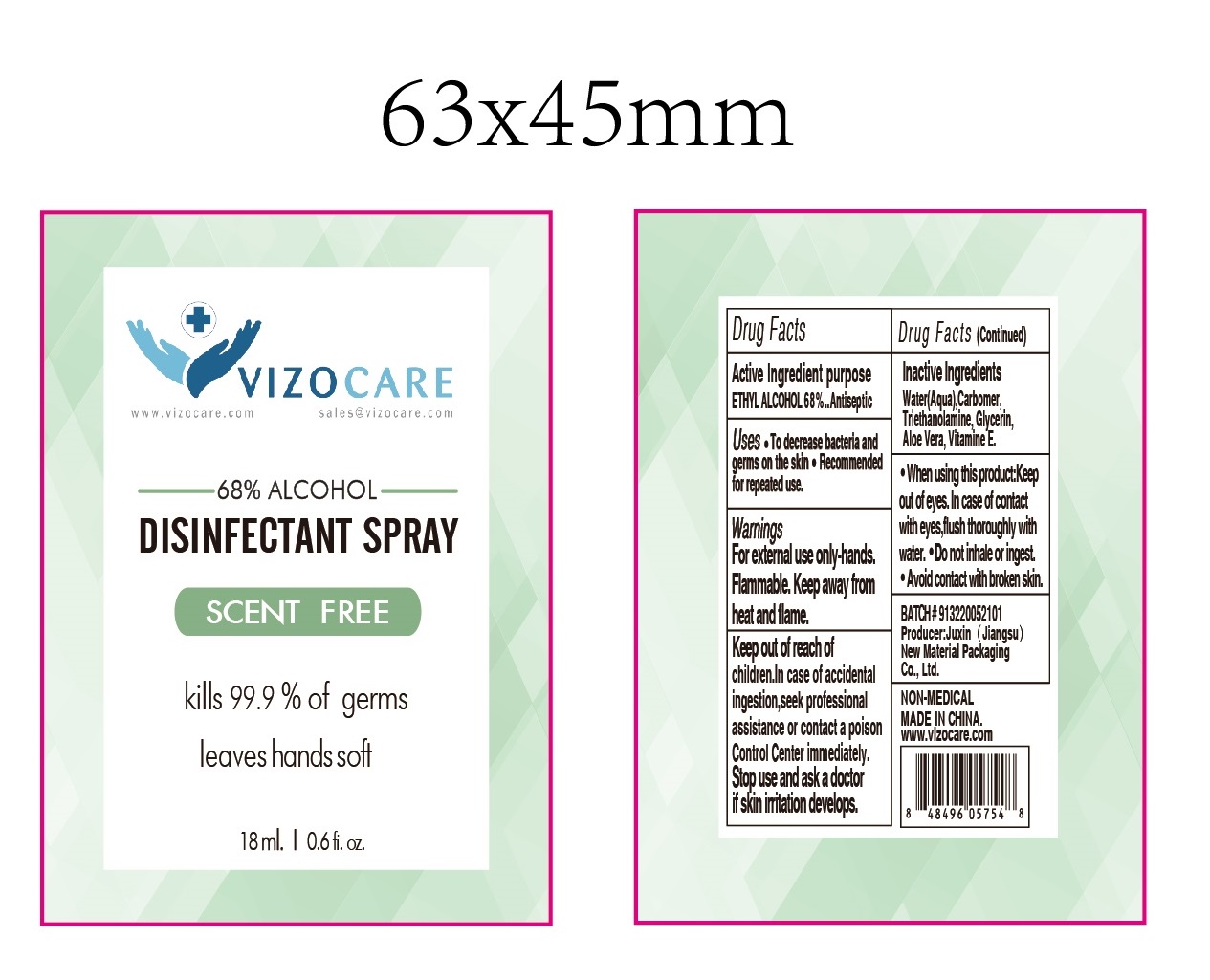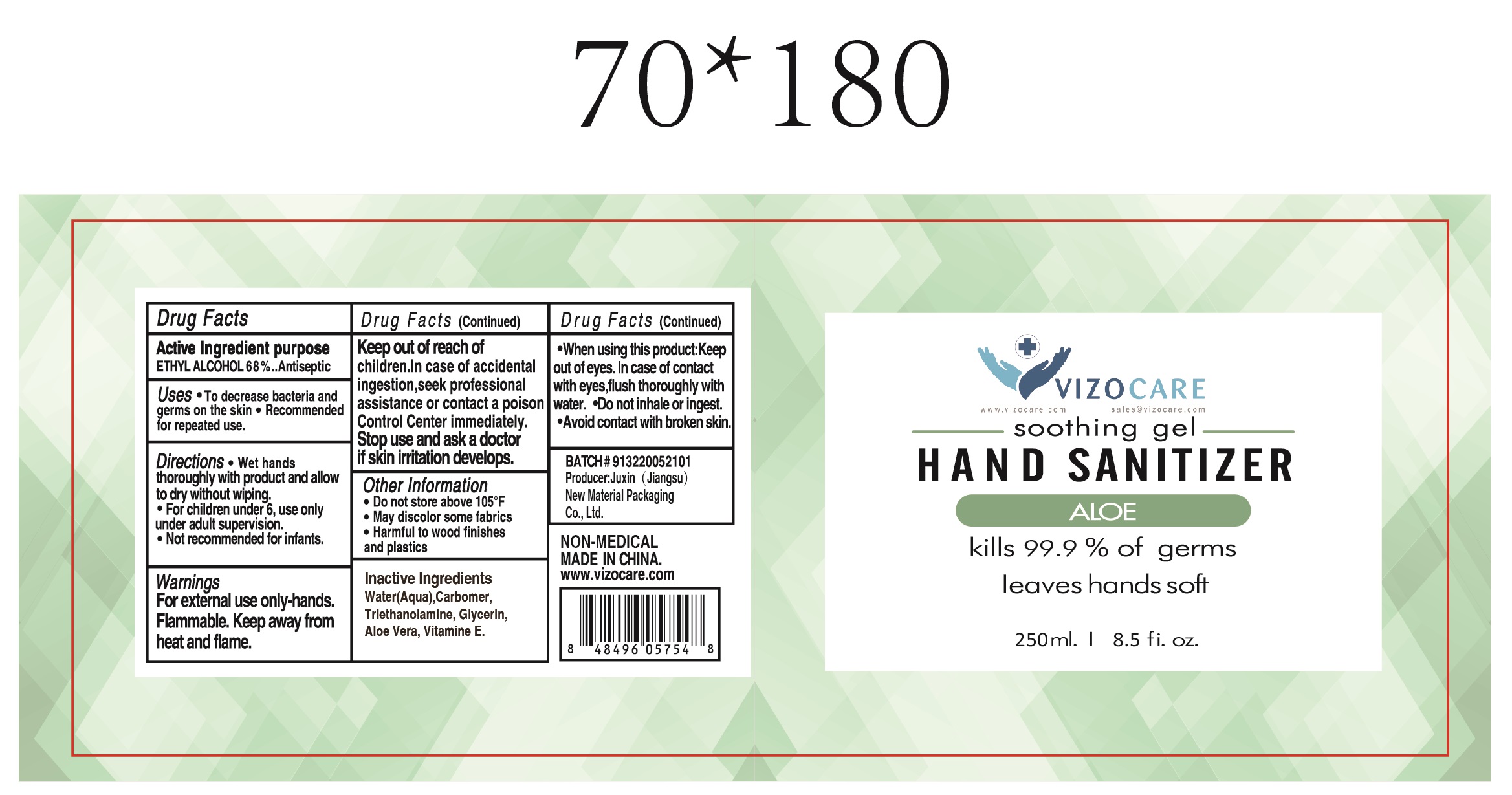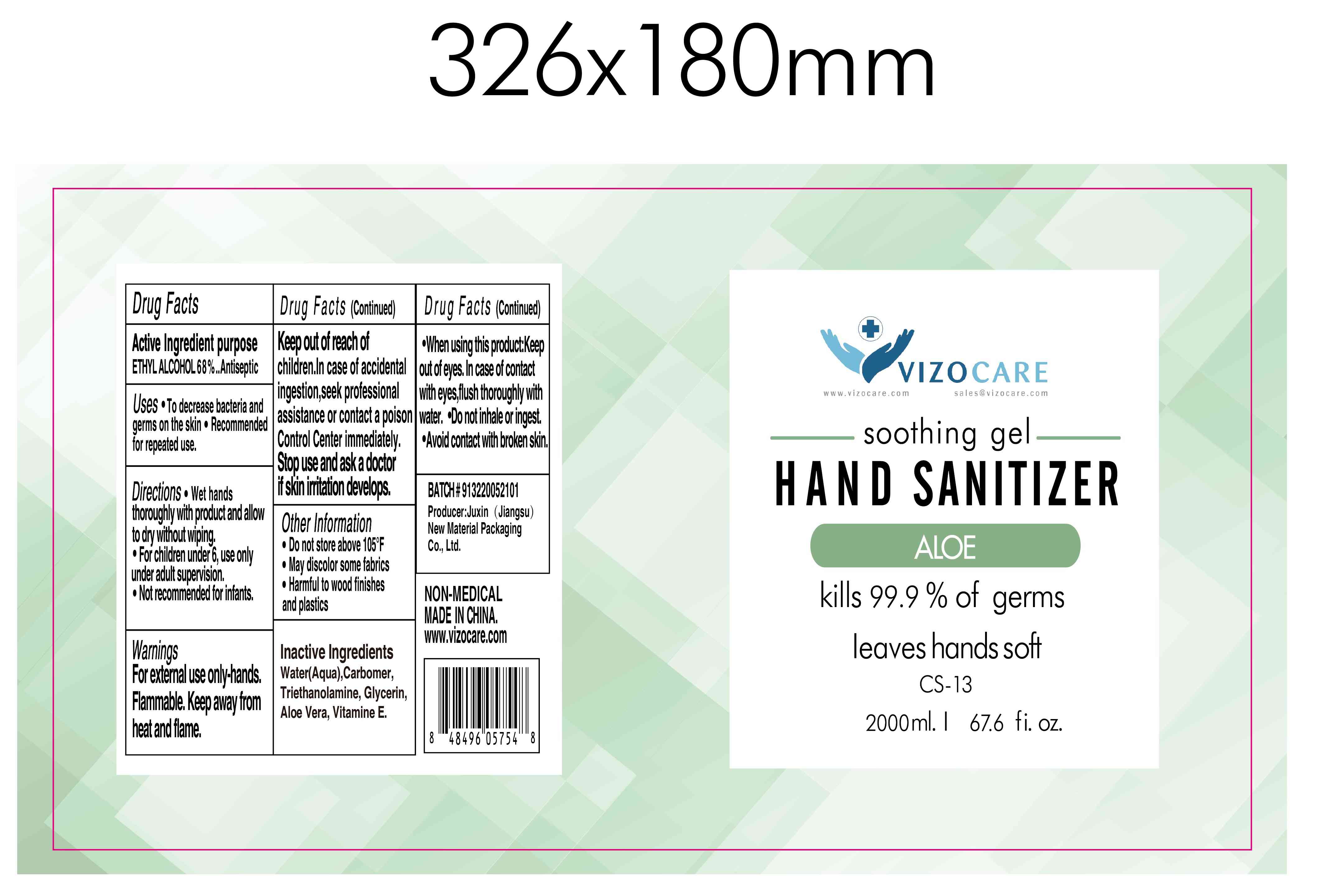 DRUG LABEL: HAND SANITIZER
NDC: 79805-001 | Form: GEL
Manufacturer: JUXIN (Jiangsu) New Material Packaging Co., Ltd.
Category: otc | Type: HUMAN OTC DRUG LABEL
Date: 20250104

ACTIVE INGREDIENTS: ALCOHOL 68 mL/100 mL
INACTIVE INGREDIENTS: TROLAMINE; ALOE VERA LEAF; GLYCERIN; CARBOMER HOMOPOLYMER, UNSPECIFIED TYPE; WATER; .ALPHA.-TOCOPHEROL SUCCINATE, D-

79805-001
HAND SANITIZER

Active Ingredient(s)

ETHYL ALCOHOL 68%

Purpose

Antiseptic

Use

To decrease bacteria and germs on the skin.
Recommendedfor repeated use

Warnings

For external use only-hands
Flammable. Keep away from heat and flame

Do not use

/

When using this product:Keep out of eyes. In case of contact with eyes, flush thoroughly with water. Do not inhale or ingest. Avoid contact with broken skin.

Stop use and ask a doctor if skin initation develops.

Keep out of reach of children, In case of accidental ingestion, see professional assistance or contact a poison Control Center immediately.

Directions

Wet hands thoroughly with product and allow to dry wthout wiping.
For children under 6, use only under adult supervision
Not recommended for infants

Other information

Do not store above 105°F
May discolor some fabrics
Harmful to wood finishes and plastics

Inactive ingredients

Water(Aqua), Carbomer, Triethanolamine, Glycerin, Aloe vera, Vitamine E.